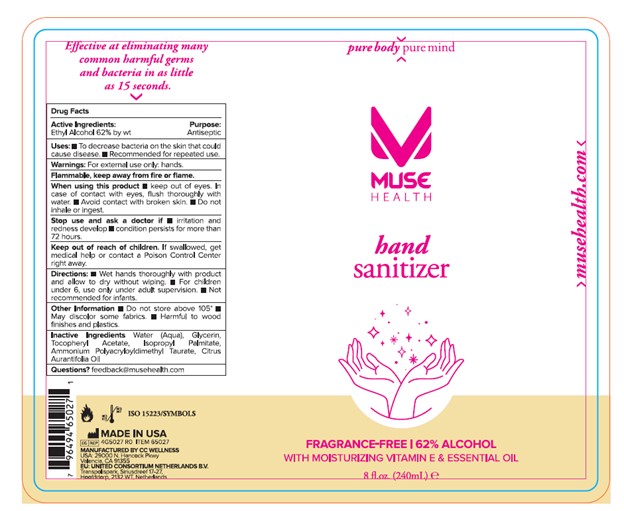 DRUG LABEL: Muse Health Hand Sanitizer - Fragrance Free
NDC: 71683-012 | Form: GEL
Manufacturer: CC Wellness, LLC
Category: otc | Type: HUMAN OTC DRUG LABEL
Date: 20220427

ACTIVE INGREDIENTS: ALCOHOL 62 mL/100 mL
INACTIVE INGREDIENTS: GLYCERIN; .ALPHA.-TOCOPHEROL ACETATE; ISOPROPYL PALMITATE; AMMONIUM POLYACRYLOYLDIMETHYL TAURATE (55000 MPA.S); WATER; LIME OIL

ACTIVE INGREDIENT

Ethyl Alcohol 62% by wt

PURPOSE

Antiseptic

Uses

To decrease bacteria on the skin that could cause disease

Recommended for repeated use.

WARNINGS

For external use only: hands

When using this product

Keep out of eyes

In case of contact with eyes, flush thoroughly with water

Avoid contact with broken skin

Do not inhale or ingest

Stop use and ask a doctor if

Irritation and redness develop

Condition persists for more than 72 hours

KEEP OUT OF REACH OF CHILDREN

If swallowed, get meidcal help or contact a Poison Control Center right away.

Directions

Wet hands thoroughly with product and allow to dry without wiping.

For children under 6, use only under adult supervision.

Not recommended for infants

Other information

Do not store above 105°

May discolor some fabrics

Harmful to wood finishes and plastics

INACTIVE INGREDIENT

Water (Aqua), Glycerin, Tocopheryl Acetate, Isopropyl Palmitate, Ammonium polyacryloyldimethyl taurate, Citrus Aurantifoila Oil

Questions?

feedback@musehealth.com